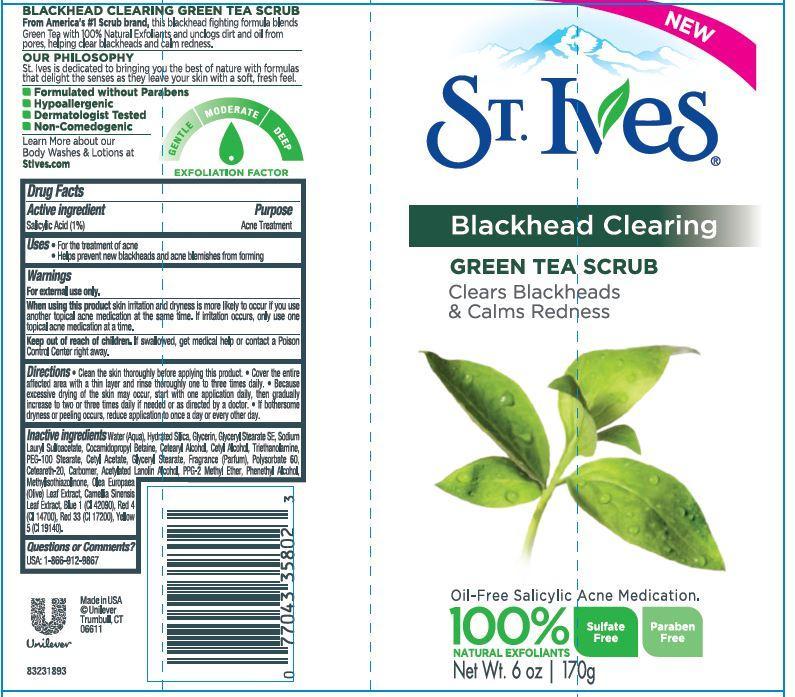 DRUG LABEL: St. Ives
NDC: 64942-1336 | Form: EMULSION
Manufacturer: CONOPCO Inc. d/b/a Unilever
Category: otc | Type: HUMAN OTC DRUG LABEL
Date: 20131106

ACTIVE INGREDIENTS: Salicylic Acid 0.01 g/1 mL
INACTIVE INGREDIENTS: WATER; HYDRATED SILICA; GLYCERIN; GLYCERYL STEARATE SE; SODIUM LAURYL SULFOACETATE; COCAMIDOPROPYL BETAINE; CETOSTEARYL ALCOHOL; CETYL ALCOHOL; TROLAMINE; PEG-100 STEARATE; CETYL ACETATE; GLYCERYL MONOSTEARATE; POLYSORBATE 60; POLYOXYL 20 CETOSTEARYL ETHER; ACETYLATED LANOLIN ALCOHOLS; PPG-2 METHYL ETHER; PHENYLETHYL ALCOHOL; OLEA EUROPAEA LEAF; METHYLISOTHIAZOLINONE; GREEN TEA LEAF; FD&C BLUE NO. 1; FD&C YELLOW NO. 5; D&C RED NO. 33; FD&C RED NO. 4

St. Ives Blackhead Clearing Green Tea Scrub

Active ingredient
Salicylic Acid (1%)

Purpose
Acne Treatment

Uses
· For the treatment of acne

· Helps prevent new blackheads and acne blemishes from forming

Warnings
For external use only.

When using this product skin irritation and dryness is more likely to occur if you use another topical acne medication at the same time. If irritation occurs, only use one topical acne medication at a time.

Keep out of reach of children. If swallowed, get medical help or contact a Poison Control Center right away.

DOSAGE AND ADMINISTRATION

Directions · Clean the skin thoroughly before applying this product. · Cover the entire affected area with a thin layer and rinse thoroughly one to three times daily. · Because excessive drying of the skin may occur, start with one application daily, then gradually increase to two or three times daily if needed or as directed by a doctor. · If bothersome dryness or peeling occurs, reduce application to once a day or every other day.

Inactive ingredients

Water (Aqua), Hydrated Silica, Glycerin, Glyceryl Stearate SE, Sodium Lauryl Sulfoacetate, Cocamidopropyl Betaine, Cetearyl Alcohol, Cetyl Alcohol, Triethanolamine, PEG-100 Stearate, Cetyl Acetate, Glyceryl Stearate, Fragrance (Parfum), Polysorbate 60, Ceteareth-20, Carbomer, Acetylated Lanolin Alcohol, PPG-2 Methyl Ether, Phenethyl Alcohol, Methylisothiazolinone, Olea Europaea (Olive) Leaf Extract, Camellia Sinensis Leaf Extract, Blue 1 (CI 42090), Red 4 (CI 14700), Red 33 (CI 17200), Yellow 5 (CI 19140).

Questions or Comments?

USA: 1-866-912-9867